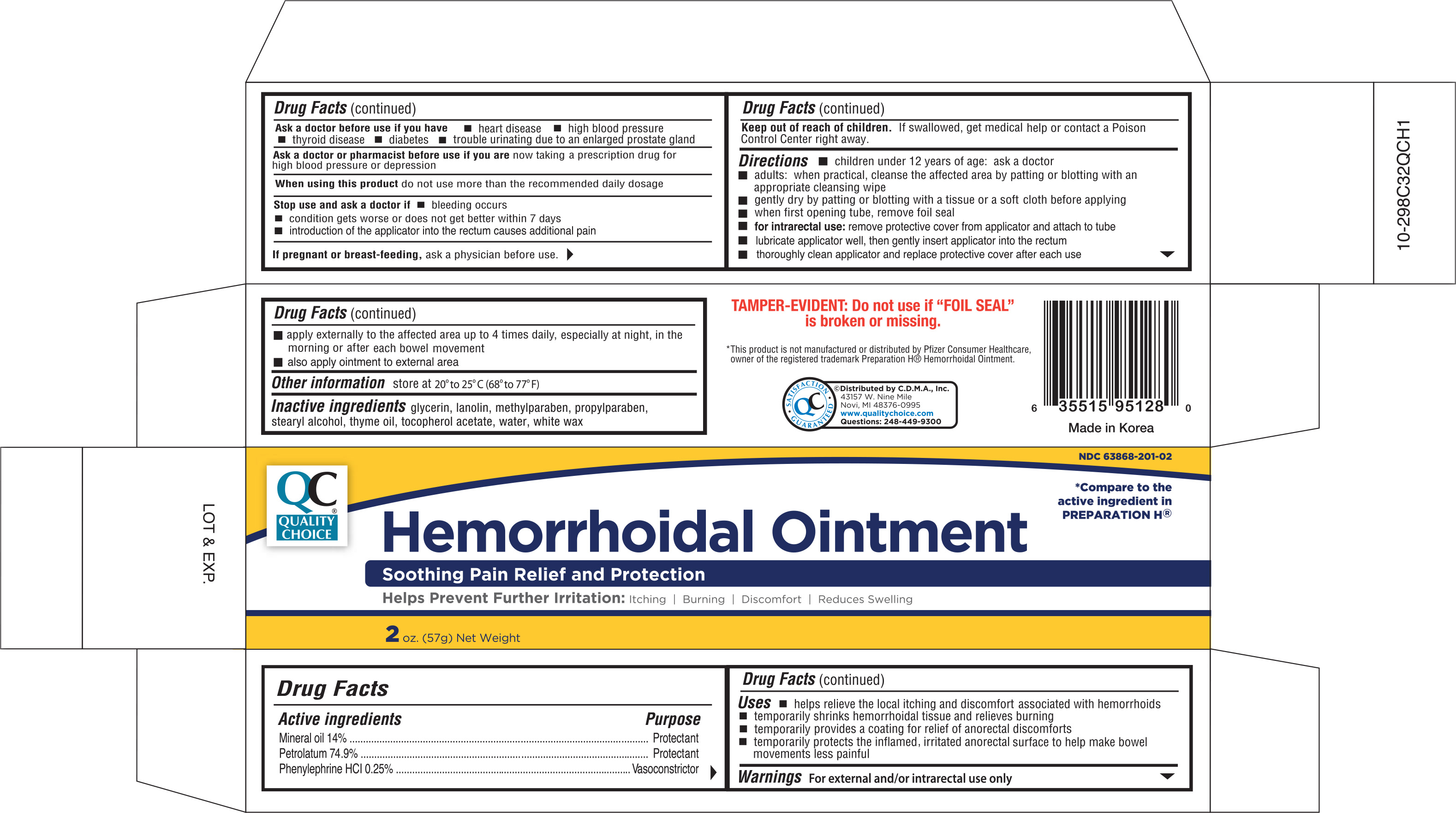 DRUG LABEL: Quality Choice Hemorrhoidal
NDC: 63868-201 | Form: OINTMENT
Manufacturer: Chain Drug Marketing Association
Category: otc | Type: HUMAN OTC DRUG LABEL
Date: 20191205

ACTIVE INGREDIENTS: MINERAL OIL 140 mg/100 g; PETROLATUM 749 mg/100 g; PHENYLEPHRINE HYDROCHLORIDE 2.5 mg/100 g
INACTIVE INGREDIENTS: GLYCERIN; LANOLIN; METHYLPARABEN; PROPYLPARABEN; STEARYL ALCOHOL; THYME OIL; ALPHA-TOCOPHEROL ACETATE; WATER; WHITE WAX

QC Hemorrhoidal Ointment 2oz (with applicator) NBE Preparation H 95128

Active ingredients Purpose

Mineral oil 14%................................................................Protectant

Petrolatum 74.9%............................................................Protectant

Phenylephrine HCl 0.25%..........................................Vasoconstrictor

Uses

- helps relieve the local itching and discomfort associated with hemorrhoids
- temporarily shrinks hemorrhoidal tissue and relieves burning
- temporarily provides a coating for relief of anorectal discomforts
- temporarily protects the inflamed, irritated anorectal surface to help make bowel movements less painful

Warnings For external and/or intrarectal use only

Ask a doctor before use if you have

- heart disease
- high blood pressure
- thyroid disease
- diabetes
- trouble urinating due to an enlarged prostate gland

Ask a doctor or a pharmacist before use if you are now taking a prescription drug for high blood pressure or depression

When using this product do not use more than the recommended daily dosage

Stop use and ask a doctor if

- bleeding occurs
- condition gets worse or does not get better within 7 days
- introduction of the applicator into the rectum causes additional pain

PREGNANCY OR BREAST FEEDING

If pregnant or breast-feeding, ask a physician before use.

Keep out of reach of children. If swallowed, get medical help or contact a Poison Control Center right away.

Directions

- children under 12 years of age: ask a doctor
- adults: when practical, cleanse the affected area by patting or blotting with an appropriate cleansing wipe
- gently dry by patting or blotting with a tissue or a soft cloth before applying
- when first opening tube, remove foil seal
- for intrarectal use: remove protective cover from applicator and attach to tube
- lubricate applicator well, then gently insert applicator into the rectum
- thoroughly clean applicator and replace protective cover after each use
- apply externally to the affected area up to 4 times daily, especially at night, in the morning or after each bowel movement
- also apply ointment to external area

Other information store at 20° to 25°C (68° to 77°F)

INACTIVE INGREDIENT

Inactive ingredients glycerin, lanolin, methylparaben, propylparaben, stearyl alcohol, thyme oil, tocopherol acetate, water, white wax

DOSAGE AND ADMINISTRATION

Distributed by:

C.D.M.A., Inc.

43157 W. Nine Mile

Novi, MI 48376-0995

www.qualitychoice.com

Made in Korea